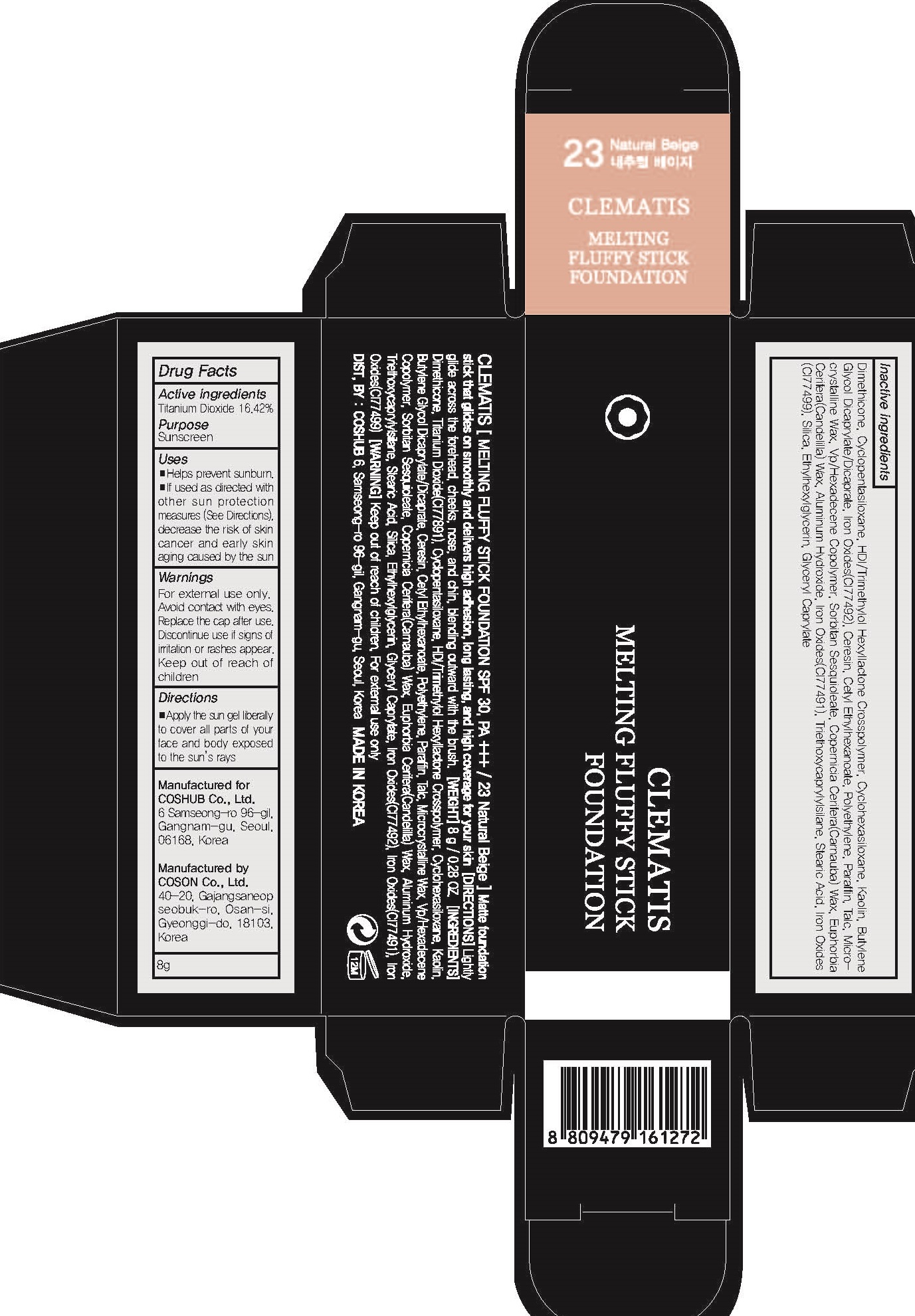 DRUG LABEL: CLEMATIS Melting Fluffy sti ck foundation 23 Natural Beige
NDC: 71702-080 | Form: STICK
Manufacturer: Coshub Co., Ltd.
Category: otc | Type: HUMAN OTC DRUG LABEL
Date: 20170905

ACTIVE INGREDIENTS: Titanium Dioxide 1.31 g/8 g
INACTIVE INGREDIENTS: Dimethicone; Kaolin

ACTIVE INGREDIENT

Active ingredients: Titanium Dioxide 16.42%

INACTIVE INGREDIENT

Inactive ingredients: Dimethicone, Cyclopentasiloxane, HDI/Trimethylol Hexyllactone Crosspolymer, Cyclohexasiloxane, Kaolin, Butylene Glycol Dicaprylate/Dicaprate, Iron Oxides(CI77492), Ceresin, Cetyl Ethylhexanoate, Polyethylene, Paraffin, Talc, Microcrystalline Wax, Vp/Hexadecene Copolymer, Sorbitan Sesquioleate, Copernicia Cerifera(Carnauba) Wax, Euphorbia Cerifera(Candelilla) Wax Aluminum Hydroxide, Iron Oxides(CI77491), Triethoxycaprylylsilane, Stearic Acid, Iron Oxides(CI77499), Silica, Ethylhexylglycerin, Glyceryl Caprylate

PURPOSE

Purpose: Sunscreen

WARNINGS

Warnings: For external use only. Avoid contact with eyes. Replace the cap after use. Discontinue use if signs of irritation or rashes appear. Keep out of reach of children.

DESCRIPTION

Uses: - Helps prevent sunburn. - If used as directed with other sun protection measures (See Directions), decrease the risk of skin cancer and early skin aging caused by the sun

Directions: Apply the sun gel liberally to cover all parts of your face and body exposed to the sun's rays.